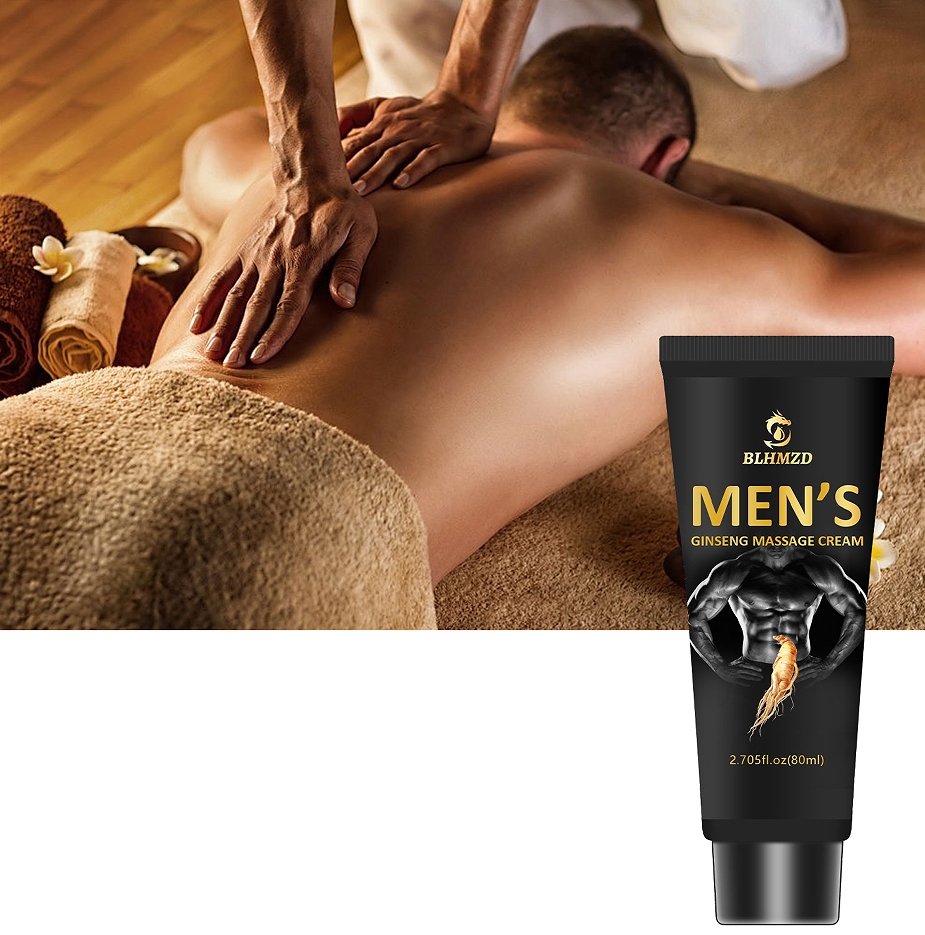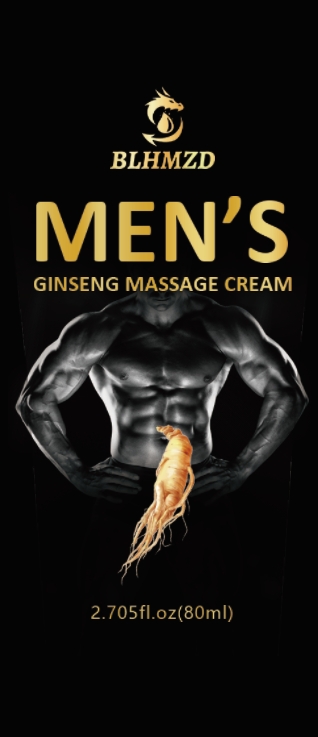 DRUG LABEL: Massage cream
NDC: 84025-310 | Form: CREAM
Manufacturer: Guangzhou Yanxi Biotechnology Co., Ltd
Category: otc | Type: HUMAN OTC DRUG LABEL
Date: 20250107

ACTIVE INGREDIENTS: RETINOL 5 mg/80 mL; HYALURONIC ACID 3 mg/80 mL
INACTIVE INGREDIENTS: WATER

WARNINGS

Keep out of children

DOSAGE AND ADMINISTRATION

Apply to affected area twice per dayon cleansed skin.Use continuously for 2-3 weeks for best results.

INACTIVE INGREDIENT

Aqua

INDICATIONS AND USAGE

For daily skin care

Keep out of children

PURPOSE

Moisturizing and massage skin